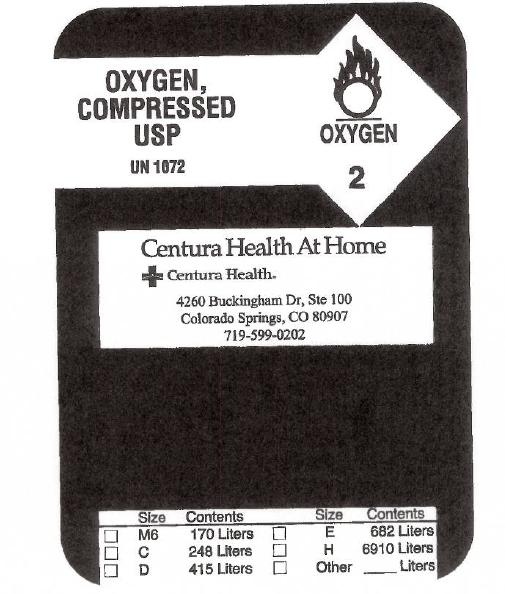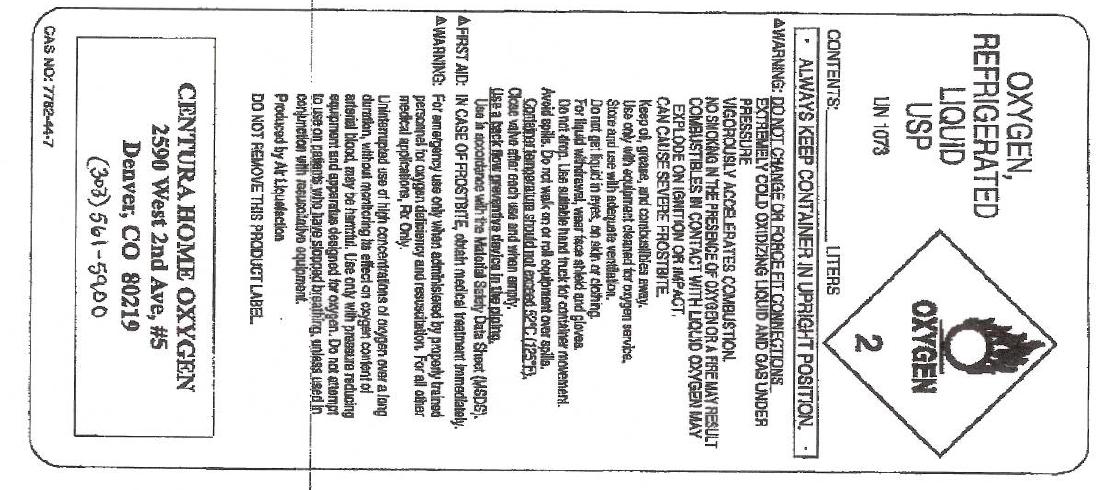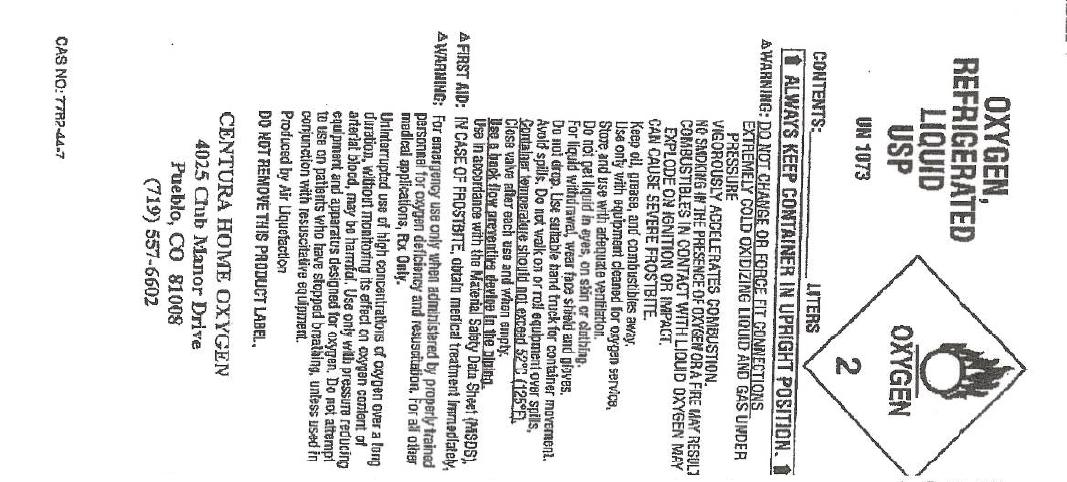 DRUG LABEL: Oxygen
NDC: 61935-001 | Form: GAS
Manufacturer: Centura Home Oxygen
Category: prescription | Type: HUMAN PRESCRIPTION DRUG LABEL
Date: 20100525

ACTIVE INGREDIENTS: Oxygen 995 mL/1 L

oxygen

PACKAGE LABEL

OXYGEN, COMPRESSED USP UN1072
OXYGEN 2
Centura Health At Home Centura Health 4260 Buckingham Dr., Ste 100 Colorado Springs, CO 80907 719-599-0202
Size Contents Size Contents
M6 170 Liters E 682 Liters
C 248 Liters H 6910 Liters
D 415 Liters Other Liters

PACKAGE LABEL

OXYGEN, REFRIGERATED LIQUID USP UN1073 CONTENTS: LITERS:
OXYGEN 2
ALWAYS KEEP CONTAINER IN UPRIGHT POSITION
WARNING: DO NOT CHANGE OR FORCEFIT CONNECTIONS. EXTREMELY COLD, OXIDIZING LIQUID AND GAS UNDER PRESSURE. VIGOROUSLY ACCELERATES COMBUSTION. COMBUSTIBLES IN CONTACT WITH LIQUID OXYGEN MAY EXPLODE ON IGNITION OR IMPACT. CAN CAUSE SEVERE FROSTBITE. Keep oil, grease, and combustibles away. Use only with equipment cleaned for oxygen service. Store and use with adequate ventilation. Do not get liquid in eyes, on skin, or clothing. For liquid withdrawal, wear face shield and gloves. Do not drop. Use suitable hand truck for container movement. Avoid spills. Do not walk on or roll equipment over spills. Container temperature should not exceed 52C (125F). Close valve after each use and when empty. Use a back flow preventive device in the piping. Use in accordance with the Material Safety Data Sheet (MSDS). FIRST AID: IN CASE OF FROSTBITE, obtain medical treatment immediately.
WARNING: For emergency use only when administered by properly trained personnel for oxygen deficiency and resuscitation. For all other medical applications, Rx Only. Uninterrupted use of high concentrations of oxygen over a long duration, without monitoring its effect on oxygen content of arterial blood, may be harmful. Use only with pressure reducing equipment and apparatus designed for oxygen. Do not attempt to use on patients who have stopped breathing, unless used in conjunction with resuscitative equipment. Produced by Air Liquefaction.
CENTURA HOME OXYGEN 2590 West 2nd Ave, #5 Denver, CO 80219 (303) 561-5900
CAS NO: 7782-44-7

PACKAGE LABEL

OXYGEN, REFRIGERATED LIQUID USP UN1073 CONTENTS: LITERS:
OXYGEN 2
ALWAYS KEEP CONTAINER IN UPRIGHT POSITION
WARNING: DO NOT CHANGE OR FORCEFIT CONNECTIONS. EXTREMELY COLD, OXIDIZING LIQUID AND GAS UNDER PRESSURE. VIGOROUSLY ACCELERATES COMBUSTION. NO SMOKING IN THE PRESENCE OF OXYGEN OR A FIRE MAY RESULT. COMBUSTIBLES IN CONTACT WITH LIQUID OXYGEN MAY EXPLODE ON IGNITION OR IMPACT. CAN CAUSE SEVERE FROSTBITE. Keep oil, grease, and combustibles away. Use only with equipment cleaned for oxygen service. Store and use with adequate ventilation. Do not get liquid in eyes, on skin, or clothing. For liquid withdrawal, wear face shield and gloves. Do not drop. Use suitable hand truck for container movement. Avoid spills. Do not walk on or roll equipment over spills. Container temperature should not exceed 52C (125F). Close valve after each use and when empty. Use a back flow preventive device in the piping. Use in accordance with the Material Safety Data Sheet (MSDS). FIRST AID: IN CASE OF FROSTBITE, obtain medical treatment immediately.
WARNING: For emergency use only when administered by properly trained personnel for oxygen deficiency and resuscitation. For all other medical applications, Rx Only. Uninterrupted use of high concentrations of oxygen over a long duration, without monitoring its effect on oxygen content of arterial blood, may be harmful. Use only with pressure reducing equipment and apparatus designed for oxygen. Do not attempt to use on patients who have stopped breathing, unless used in conjunction with resuscitative equipment. Produced by Air Liquefaction. DO NOT REMOVE THIS PRODUCT LABEL.
CENTURA HOME OXYGEN 4025 Club Manor Drive Pueblo, CO 81008 (719) 557-6602
CAS NO: 7782-44-7